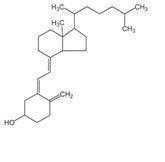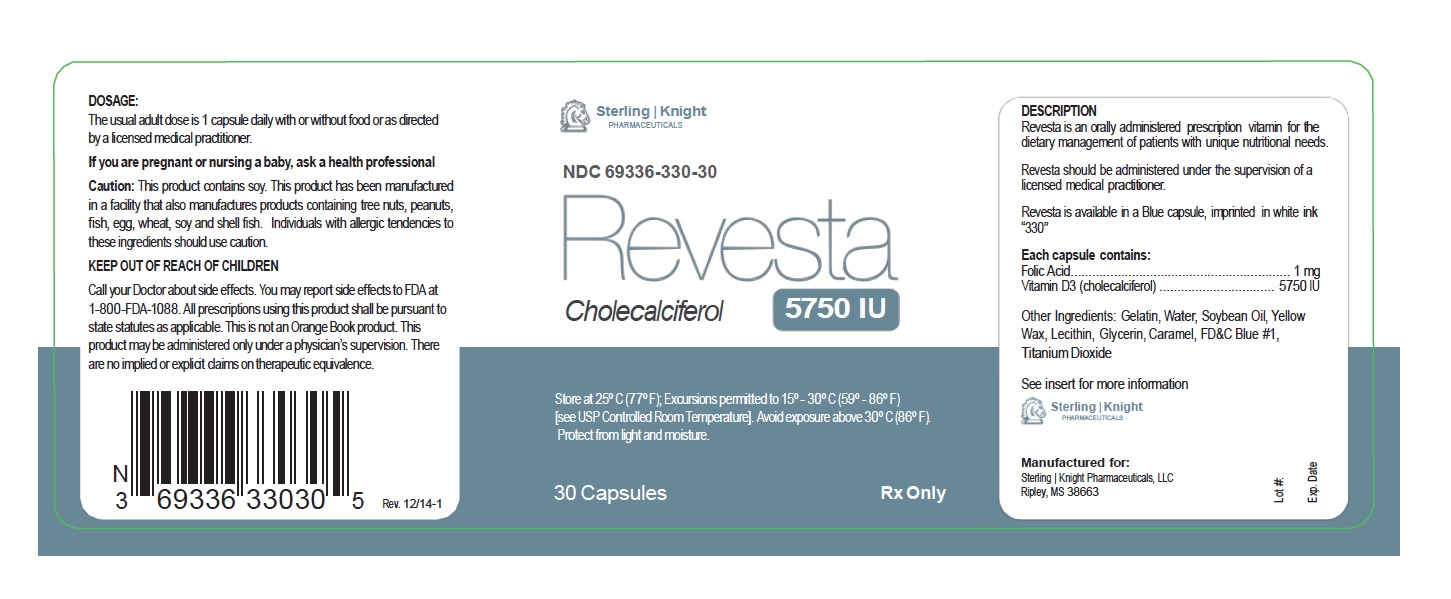 DRUG LABEL: Revesta
NDC: 69336-330 | Form: CAPSULE
Manufacturer: Sterling Knight Pharmaceuticals,LLC
Category: prescription | Type: HUMAN PRESCRIPTION DRUG LABEL
Date: 20191216

ACTIVE INGREDIENTS: CHOLECALCIFEROL 5750 [iU]/1 1; FOLIC ACID 1 mg/1 1
INACTIVE INGREDIENTS: WATER; SOYBEAN OIL; YELLOW WAX; LECITHIN, SOYBEAN; FD&C BLUE NO. 1; GLYCERIN; TITANIUM DIOXIDE; GELATIN

Revesta
Cholecalciferol Capsules
Rx Only

DESCRIPTION

Revesta is an orally administered prescription Vitamin for the dietary management of patients with unique nutritional needs requiring increased folate levels, Vitamin D supplementation due to Vitamin D deficiency and other nutritional supplementation.

Revesta should be administered under the supervision of a licensed medical practitioner.

Vitamin D3 (cholecalciferol) is a white, crystalline powder, very soluble in water, with the following structural formula:

Each capsule contains:
Folic Acid: 1mg, Vitamin D3 (Cholecalciferol): 5750IU

Each capsule contains the following inactive ingredients: soybean oil, gelatin (bovine), yellow wax, glycerin, deionized water, lecithin, titanium dioxide, FD&C Blue #1.

INDICATIONS AND USAGE

Revesta is indicated for dietary management of patients with unique nutritional needs requiring increased folate levels, Vitamin D deficiency or are in need of Vitamin D supplementation and other nutritional supplementation.

CLINICAL PHARMACOLOGY

The in vivo synthesis of the major biologically active metabolites of vitamin D occurs in two steps. The first hydroxylation of ergocalciferol takes place in the liver (to 25-hydroxyvitamin D) and the second in the kidneys (to 1,25-dihydroxyvitamin D). Vitamin D metabolites promote the active absorption of calcium and phosphorus by the small intestine, thus elevating serum calcium and phosphate levels sufficiently to permit bone mineralization. Vitamin D metabolites also mobilize calcium and phosphate from bone and probably increase the reabsorption of calcium and perhaps also of phosphate by the renal tubules.

There is a time lag of 10 to 24 hours between the administration of vitamin D and the initiation of its action in the body due to the necessity of synthesis of the active metabolites in the liver and kidneys. Parathyroid hormone is responsible for the regulation of this metabolism in the kidneys.

CONTRAINDICATIONS

This product is contraindicated in patients with a known hypersensitivity to any of the ingredients. Revesta is contraindicated in patients with hypercalcemia, malabsorption syndrome, abnormal sensitivity to the toxic effects of vitamin D, and hypervitaminosis D.

WARNINGS AND PRECAUTIONS

Tell your doctor if you have: kidney problems, thyroid disease. This medication should be used as directed during pregnancy or while breast-feeding. Consult your doctor about the risks and benefits.

Folic acid alone is improper therapy in the treatment of pernicious anemia and other megaloblastic anemias where vitamin B12 is deficient. Folic acid in doses above 1 mg daily may obscure pernicious anemia in that hematologic remission can occur while neurological manifestations progress.

ADVERSE REACTIONS

This medication is generally well tolerated. Notify your doctor if you experience: nausea, loss of appetite, vomiting, stomach cramps, dry mouth, increased thirst, increased urination, muscle or bone pain,headache, weakness, weight loss, dizziness. If you notice other effects not listed above, contact your doctor or pharmacist.

DOSAGE AND ADMINISTRATION

Take one capsule daily or as directed by a physician.

HOW SUPPLIED

Revesta capsules are supplied as blue capsules imprinted in white ink “330”, dispensed in HDPE plastic bottles of 30ct.

STORAGE AND HANDLING SECTION

Store at controlled room temperature 15°-30°C (59°F-86°F). Keep in cool dry place.

Call your doctor about side effects. You may report side effects to FDA at 1-800-FDA-1088.

KEEP THIS AND ALL DRUGS OUT OF THE REACH OF CHILDREN.

OTHER SAFETY INFORMATION

Reserved for Professional Recommendation

All prescriptions using this product shall be pursuant to state statutes as applicable. This is not an Orange Book product. This product may be administered only under a physician’s supervision. There are no implied or explicit claims on therapeutic equivalence.

PACKAGE LABEL. PRINCIPAL DISPLAY PANEL

Rx Only
Reserved for Professional Recommendation
All prescriptions using this product shall be pursuant to state statutes as applicable. This is not an Orange Book product. This product may be administered only under a physician’s supervision. There are no implied or explicit claims on therapeutic equivalence.

Manufactured for:Sterling Knight Pharmaceuticals, LLC
Ripley, MS 38663
Rev. 1114-1